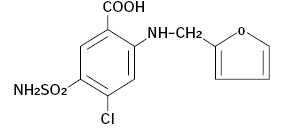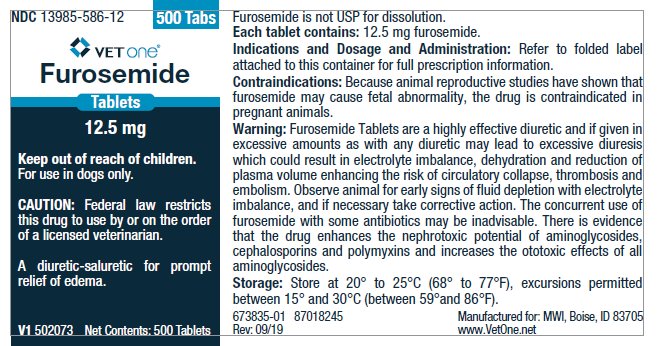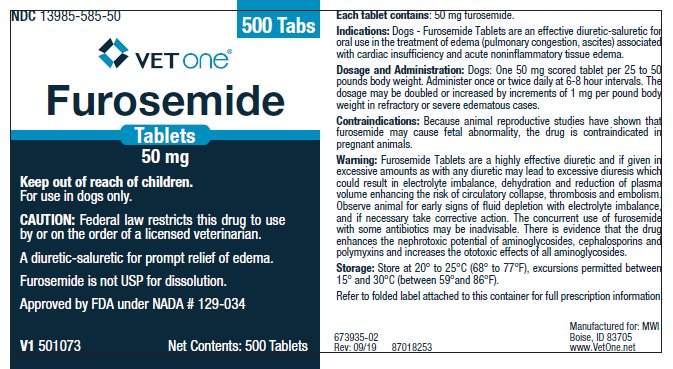 DRUG LABEL: Furosemide
NDC: 13985-586 | Form: TABLET
Manufacturer: MWI/VetOne
Category: animal | Type: PRESCRIPTION ANIMAL DRUG LABEL
Date: 20250429

ACTIVE INGREDIENTS: FUROSEMIDE 12.5 mg/1 1
INACTIVE INGREDIENTS: DIBASIC CALCIUM PHOSPHATE DIHYDRATE; MICROCRYSTALLINE CELLULOSE; POVIDONE K30; SODIUM STARCH GLYCOLATE TYPE A POTATO; MAGNESIUM STEARATE

Furosemide Tablets

Approved by FDA under NADA # 129-034

Furosemide is not USP for dissolution.

For use in dogs only.

Caution:

Federal law restricts this drug to use by or on the order of a licensed veterinarian.

Description:

Furosemide is a potent loop diuretic which is a derivative of anthranilic acid. The structure is:

Chemical Name: 4-Chloro-N-furfuryl-5-sulfamoylanthranilic acid.

Furosemide is pharmacodynamically characterized by the following:

1) It is administered orally. It is easily absorbed from the intestinal tract and begins to act in 30 to 60 minutes after oral administration.^(1, 2)

2) Is a loop diuretic which inhibits reabsorption of sodium and chloride at the ascending loop of Henle in the kidneys, enhancing water excretion. ^3

3) A dose-response relationship and a ratio of minimum to maximum effective dose range greater than tenfold. ^1

4) A high degree of efficacy, low inherent toxicity and a high therapeutic index.

Actions:

The therapeutic efficacy of Furosemide Tablets is from the activity of the intact and unaltered molecule throughout the nephron, inhibiting the reabsorption of sodium not only in the proximal and distal tubule but also in the ascending limb of the loop of Henle. The prompt onset of action is a result of the drug's rapid absorption and a poor lipid solubility. The low lipid solubility and a rapid renal excretion minimize the possibility of its accumulation in tissues and organs or crystalluria. Furosemide Tablets have no inhibitory effect on carbonic anhydrase or aldosterone activity in the distal tubule. The drug possesses diuretic activity either in the presence of acidosis or alkalosis.^(1, 2, 4, 5, 6)

Indications:

Dogs - Furosemide Tablets are indicated for the treatment of edema (pulmonary congestion, ascites) associated with cardiac insufficiency and acute non-inflammatory tissue edema. In cases of edema involving cardiac insufficiency, the continued use of heart stimulants such as digitalis or its glycosides is indicated. The rationale for efficacious use of diuretic therapy is determined by the clinical pathology producing the edema.

Dosage and Administration:

The usual oral dosage of Furosemide Tablets is 1 to 2 mg/lb body weight (approximately 2.5 to 5 mg/kg). A prompt diuresis usually ensues from the initial treatment.

Administer orally once or twice daily at 6 to 8 hour intervals. The dosage should be adjusted to the individual's response. In severe edematous or refractory cases, the dose may be doubled or increased by increments of 1.0 mg per pound of body weight. The established effective dose should be administered once or twice daily. The daily schedule of administration can be timed to control the period of micturition for the convenience of the client or veterinarian. Mobilization of the edema may be most efficiently and safely accomplished by utilizing an intermittent daily dose schedule, i.e., every other day or 2 to 4 consecutive days weekly.

Diuretic therapy should be discontinued after reduction of the edema, or maintained after determining a carefully programmed dosage schedule to prevent recurrence of edema. For long-term treatment, the dose can generally be lowered after the edema has once been reduced. Re-examination and consultations with the client will enhance the establishment of a satisfactorily programmed dosage schedule. Clinical examination and serum BUN, CO2 and electrolyte determinations should be performed during the early period of therapy and periodically thereafter, especially in refractory cases. Abnormalities should be corrected or the drug temporarily withdrawn.

Dosage: Oral

Dog: One-half to one 50 mg scored tablet per 25 pounds body weight. One 12.5 mg scored tablet per 5 to 10 pounds body weight.

Administer once or twice daily, permitting a 6- to 8-hour interval between treatments. In refractory or severe edematous cases, the dosage may be doubled or increased by increments of 1 mg per pound body weight as recommended in preceding paragraphs, "Dosage and Administration".

Contraindications:

Animal reproductive studies have shown that furosemide may cause fetal abnormality and the drug is contraindicated in pregnant animals. Furosemide is contraindicated in anuria, furosemide hypersensitivity, hepatic coma, or during electrolytic imbalances. Monitor serum electrolytes, BUN and CO2 frequently. Monitor serum potassium levels and watch for signs of hypocalcemia.

Corticosteroids cause an additive potassium-depletion effect.

Warnings:

Furosemide Tablets are a highly effective diuretic and, if given in excessive amounts, as with any diuretic, may lead to excessive diuresis which could result in electrolyte imbalance, dehydration and reduction of plasma volume, enhancing the risk of circulatory collapse, thrombosis and embolism. Therefore, the animal should be observed for early signs of fluid depletion with electrolyte imbalance, and corrective measures administered. Excessive loss of potassium in patients receiving digitalis or its glycosides may precipitate digitalis toxicity. Caution should be exercised in animals administered potassium-depleting steroids. Correct potassium deficiency with proper dietary supplementation. If animal needs potassium supplements, use oral liquid form, do not use enteric-coated potassium tablets.

The concurrent use of furosemide with some antibiotics may be inadvisable. There is evidence that the drug enhances the nephrotoxic potential of aminoglycosides, cephalosporins and polymyxins and increases the ototoxic effects of all aminoglycosides.

Sulfonamide diuretics have been reported to decrease arterial responsiveness to pressor amines and to enhance the effect of tubocurarine. Caution should be exercised in administering curare or its derivatives to patients undergoing therapy with Furosemide Tablets and it is advisable to discontinue Furosemide Tablets for one day prior to any elective surgery.

Precautions:

Furosemide Tablets are a highly effective diuretic-saluretic which, if given in excessive amounts, may result in dehydration and electrolyte imbalance. Therefore, the dosage and schedule may have to be adjusted to the patient's need. The animal should be observed for early signs of electrolyte imbalance, and corrective measures administered. Early signs of electrolyte imbalance are increased thirst, lethargy, drowsiness or restlessness, fatigue, oliguria, gastrointestinal disturbances and tachycardia. Special attention should be given to potassium levels. Furosemide Tablets may lower serum calcium levels and cause tetany in rare cases of animals having an existing hypocalcemic tendency. ^(7, 8, 9, 10, 11)

Furosemide Tablets are contraindicated in anuria. Therapy should be discontinued in cases of progressive renal disease if increasing azotemia and oliguria occur during the treatment. Sudden alterations of fluid and electrolyte imbalance in an animal with cirrhosis may precipitate hepatic coma, therefore, observation during period of therapy is necessary. In hepatic coma and in states of electrolyte depletion, therapy should not be instituted until the basic condition is improved or corrected. Potassium supplementation may be necessary in cases routinely treated with potassium-depleting steroids.

Active or latent diabetes may on rare occasions be exacerbated by furosemide. Transient loss of auditory capacity has been experimentally produced in cats following intravenous injections of excessive doses of furosemide at a very rapid rate. ^(12, 13, 14)

Animal Safety:

Furosemide demonstrates a very low order of either acute or chronic toxicity. The drug is rapidly absorbed and excreted by both glomerular filtration and tubular secretion. The rates of excretion are of such magnitude that cumulation of furosemide does not occur despite repeated administrations. ^15

The main effect observed in clinical toxicity is an abnormality of fluid and electrolyte imbalances. Ototoxicity resulting in transient loss of hearing has been reported with furosemide. ^15

A safety study was performed in dogs to determine the effects of Furosemide Tablets at increasing dosages and time elements. The dosage levels were 2 mg/lb body weight (upper recommended dosage), 6 mg/lb body weight (3X upper recommended dosage) and 10 mg/lb body weight (5X upper recommended dosage). The treatment period ranged up to nine days in length. Results demonstrate a mild dehydration at the 5X level with a slight elevation of hemoglobin and hematocrit levels. Serum levels of potassium and chloride were slightly lowered in the higher dosage groups. Cumulative evaluation of the data demonstrates that Furosemide Tablets are safe when administered at the upper level of the recommended dosage for a duration of nine consecutive days.

To report suspected adverse events, for technical assistance, or to obtain a copy of the Safety Data Sheet, call 1-888-637-4251.

For additional information about adverse drug experience reporting for animal drugs, contact FDA by telephone at 1-888-FDA-VETS or online at www.fda.gov/reportanimalae.

Storage:

Store at 20° to 25°C (68° to 77°F), excursions permitted between 15° and 30°C (between 59° and 86°F).

How Supplied:

Furosemide Tablets are available in 12.5 mg and 50 mg strength and supplied in bottles containing 500 tablets.

NDC 13985-586-12 - 12.5 mg – 500 tablets

NDC 13985-585-50 - 50 mg – 500 tablets

References:

1. Timmerman, R.J., F.R. Springman and R.K. Thoms, 1964. Evaluation of Furosemide, a New Diuretic Agent. Current Therapeutic Research, 6(2):88-94.
2. Martindale, The Extra Pharmacopoeia. 27th ed. June 1977, The Pharmaceutical Press, London, 556.
3. Suki, W., F.C. Rector, Jr. and D.W. Seldin, 1965. The Site of Action of Furosemide and Other Sulfonamide Diuretics in the Dog. Journal of Clinical Investigation, 44(9):1458-1469.
4. Berman, L.B. and A. Ebrahimi. February 1965. Experiences with Furosemide in Renal Disease. Proceedings in the Society for Experimental Biology and Medicine, 118:333-336.
5. Schmidt, H.A.E. Animal Experiments with S35 Tagged Lasix® in Canine and Ovine. Radio-chemical Pharmacological Laboratory, Farbwerke Hoechst, Frankfurt, West Germany.
6. Haussler, A. and P. Hajdu. Methods Biological Identification and Results of Studies on Absorption, Elimination and Metabolism. Research Laboratories, Farbwerke Hoechst, Frankfurt, West Germany.
7. Antoniou, L.D., G.M. Eisner, L.M. Slotkoff and L.S. Lilienfield. December 1967. Sodium and Calcium Transport in the Kidney. Clinical Research, 15(4):476.
8. Duarte, C.G. April 1967. Effects of Furosemide (F) and Ethacrynic Acid (ETA) on the Renal Clearance of Phosphate (Cp), Ultrafilterable Calcium (CUfCa) and Magnesium (CUfMg). Clinical Research, 15(2):357.
9. Duarte, C.G. October 1968. Effects of Ethacrynic Acid and Furosemide on Urinary Calcium, Phosphate and Magnesium. Metabolism, 17:867-876.
10. Nielsen, S.P., O. Andersen and K.E. Steven, 1969. Magnesium and Calcium Metabolism during Prolonged Furosemide (Lasix®) Administration to Normal Rats. Acta Pharmacol, et. Toxicol., 27:469-479.
11. Reimold, E.W. July 1972. The Effect of Furosemide on Hypercalcemia Due to Dihydrotachysterol, Metabolism, 21(7).
12. Brown, R.D. and T.W. McElwee, Jr. Effects of Intra-Arterially and Intravenously Administered Ethacrynic Acid and Furosemide on Cochlear N1 in Cats. Toxicology and Applied Pharmacology, 22:589-594, 1972.
13. Mathog, R.H., W.G. Thomas and W.R. Hudson: Ototoxicity of New and Potent Diuretics. Archives of Otolaryngology, 92(1):7-13, July 1970.
14. Mathog, R.H. and G.J. Matz: Ototoxic Effects of Ethacrynic Acid. Annals of Otolaryngology, Vol. 81, 1972.
15. Gilman, A.G., L.S. Goodman and A. Gilman,1980. The Pharmacological Basis of Therapeutics, Sixth ed., MacMillan Publishing Co., Inc., New York, NY, 903-907.

673835-01 / 673935-02

87018245 / 87018253

Rev. 09/19 / Rev. 09/19

Distributed by: MWI, Boise, ID 83705

www.VetOne.net

Principal Display Panel – Container Label, 12.5 mg 500 tablets

NDC 13985-586-12 500 Tabs

VETONE®

Furosemide Tablets 12.5 mg

Keep out of reach of children.

For use in dogs only

CAUTION: Federal law restricts this drug to use by or on the order of a licensed veterinarian.

A diuretic-saluretic for prompt relief of edema

V1 502073 Net Contents: 500 Tablets

Principal Display Panel – Container Label, 50 mg 500 tablets

NDC 13985-585-50 500 Tabs

VETONE®

Furosemide Tablets 50 mg

Keep out of reach of children.

For use in dogs only

CAUTION: Federal law restricts this drug to use by or on the order of a licensed veterinarian.

A diuretic-saluretic for prompt relief of edema

Furosemide is not USP for dissolution.

NADA 129-034, Approved by FDA

V1 501073 Net Contents: 500 Tablets